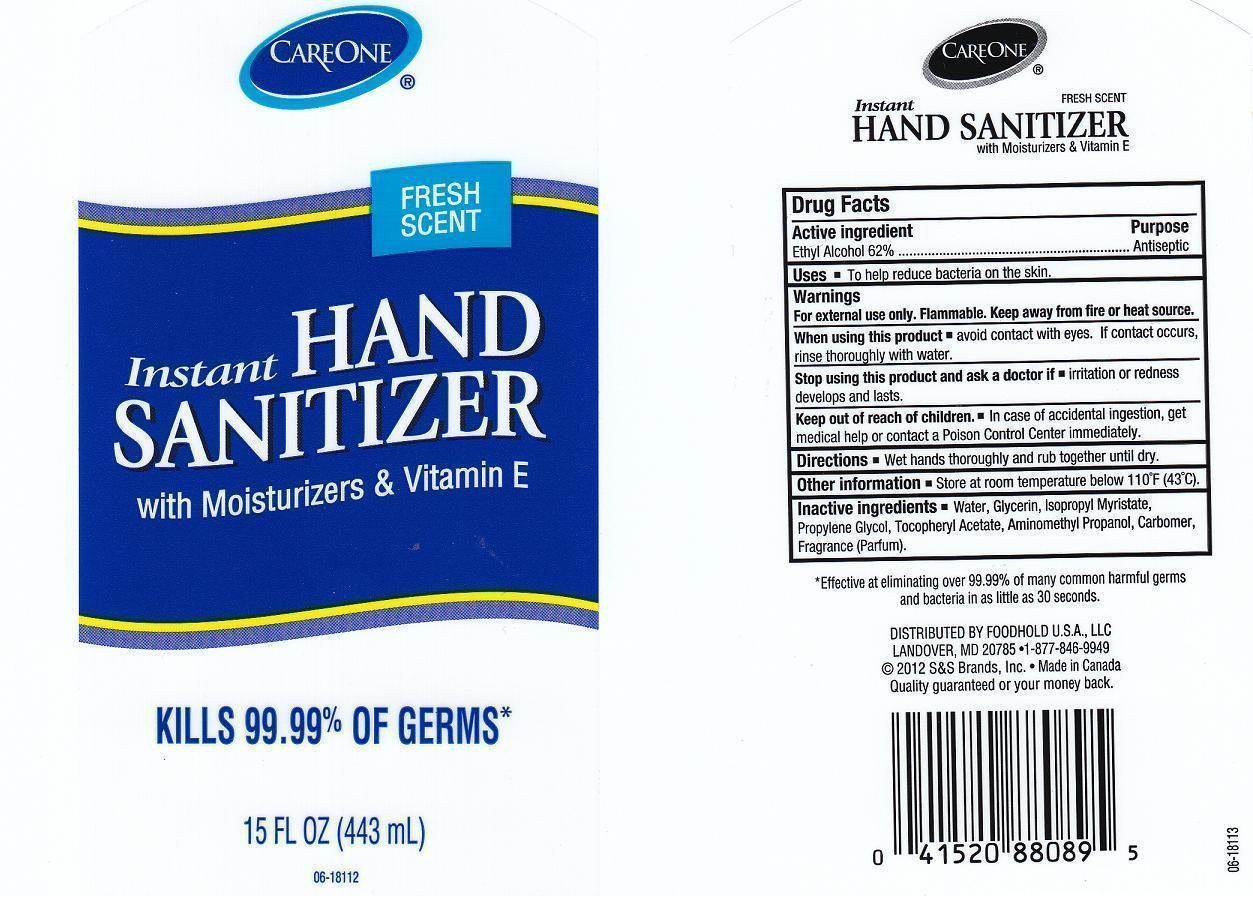 DRUG LABEL: INSTANT HAND SANITIZER
NDC: 41520-225 | Form: GEL
Manufacturer: AMERICAN SALES COMPANY
Category: otc | Type: HUMAN OTC DRUG LABEL
Date: 20130201

ACTIVE INGREDIENTS: ALCOHOL 62 mL/100 mL
INACTIVE INGREDIENTS: WATER; GLYCERIN; ISOPROPYL MYRISTATE; PROPYLENE GLYCOL; .ALPHA.-TOCOPHEROL ACETATE, D-; AMINOMETHYLPROPANOL; CARBOMER 934

DRUG FACTS

ACTIVE INGREDIENT

ETHYL ALCOHOL 62%

USES

TO HELP REDUCE BACTERIA ON THE SKIN.

WARNINGS

FOR EXTERNAL USE ONLY.

WHEN USING THIS PRODUCT

- AVOID CONTACT WITH EYES. IF CONTACT OCCURS, RINSE EYES THOROUGHLY WITH WATER.

STOP USING THIS PRODUCT AND ASK DOCTOR IF

- IRRITATION OR RASH DEVELOPS AND LASTS.

KEEP OUT OF REACH OF CHILDREN

IF SWALLOWED, GET MEDICAL HELP OR CONTACT A POISON CONTROL CENTER RIGHT AWAY.

DIRECTIONS

- APPLY A SMALL AMOUNT IN YOUR PALM AND RUB HANDS TOGETHER BRISKLY UNTIL DRY.
- CHILDREN UNDER 6 SHOULD BE SUPERVISED WHEN USING THIS PRODUCT.

OTHER INFORMATION

DO NOT STORE ABOVE 110OC (43 OC). MAY DISCOLOR CERTAIN FABRICS OR SURFACES.

PURPOSE

ANTISEPTIC

INACTIVE INGREDIENTS

WATER, GLYCERIN, ISOPROPYL MYRISTATE, PROPYLENE GLYCOL, TOCOPHERYL ACETATE, AMINOMETHYL PROPANOL, CARBOMER, FRAGRANCE.